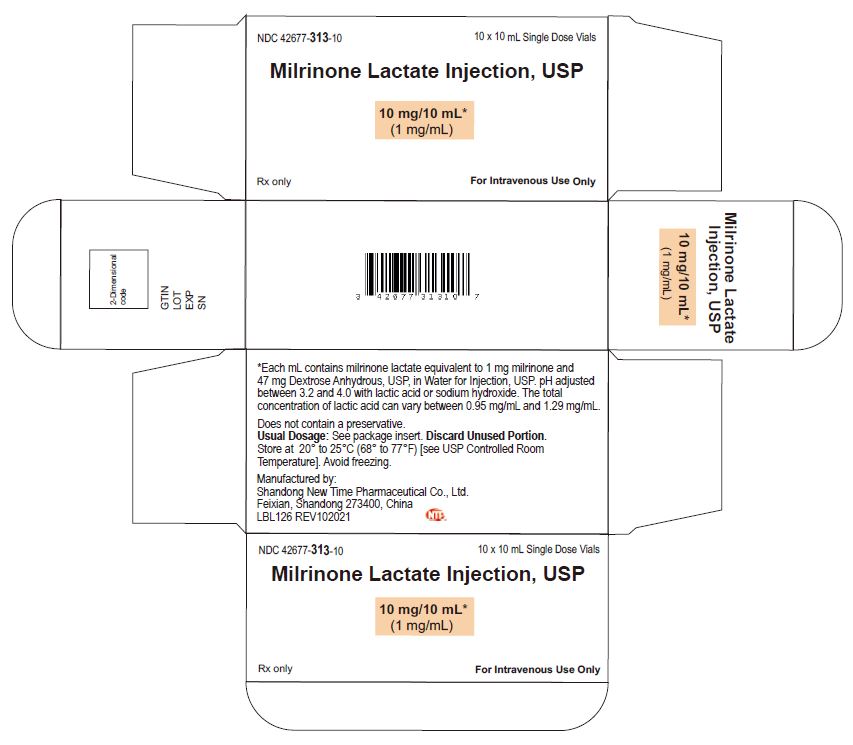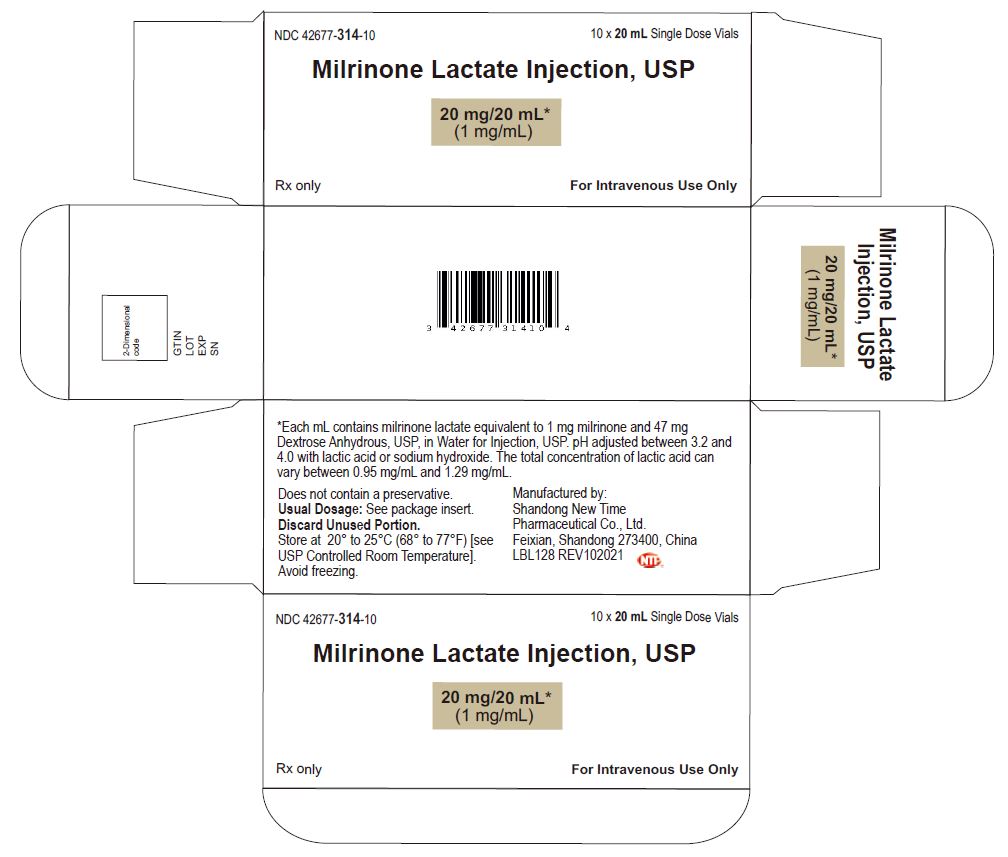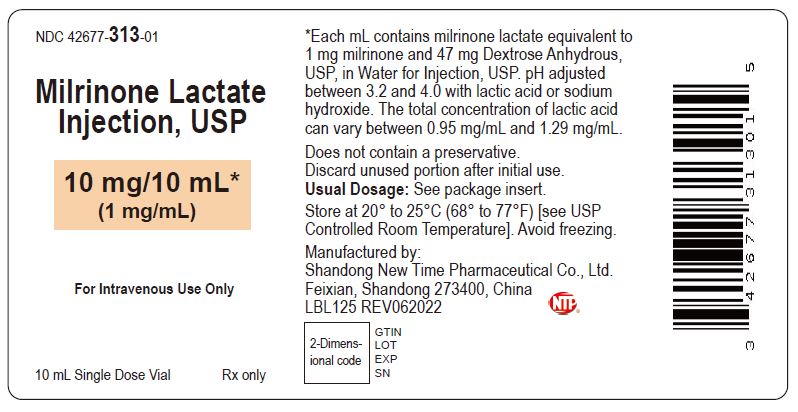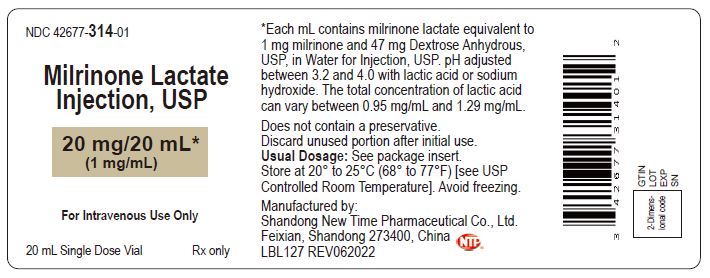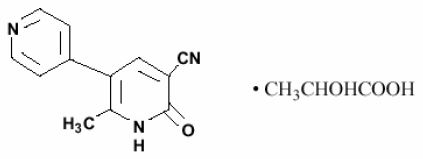 DRUG LABEL: Milrinone Lactate
NDC: 42677-313 | Form: INJECTION, SOLUTION
Manufacturer: Shandong New Time Pharmaceutical Co., Ltd.
Category: prescription | Type: HUMAN PRESCRIPTION DRUG LABEL
Date: 20260106

ACTIVE INGREDIENTS: MILRINONE LACTATE 1 mg/1 mL
INACTIVE INGREDIENTS: ANHYDROUS DEXTROSE 47 mg/1 mL; LACTIC ACID; SODIUM HYDROXIDE; WATER

Milrinone Lactate Injection, USP

DESCRIPTION

Milrinone lactate injection is a member of a class of bipyridine inotropic/vasodilator agents with phosphodiesterase inhibitor activity, distinct from digitalis glycosides or catecholamines. Milrinone lactate is designated chemically as 1,6-dihydro-2-methyl-6-oxo-[3,4'-bipyridine]-5-carbonitrile lactate and has the following structure:

Milrinone is an off-white to tan crystalline compound with a molecular weight of 211.2 and an empirical formula of C12H9N3O. It is slightly soluble in methanol, and very slightly soluble in chloroform and in water. As the lactate salt, it is stable and colorless to pale yellow in solution. Milrinone lactate is available as sterile aqueous solutions of the lactate salt of milrinone for injection or infusion intravenously.

Sterile, single-dose vials: Single-dose vials of 10 and 20 mL contain in each mL milrinone lactate equivalent to 1 mg milrinone and 47 mg Dextrose, Anhydrous, USP, in Water for Injection, USP. The pH is adjusted to between 3.2 and 4.0 with lactic acid or sodium hydroxide. The total concentration of lactic acid can vary between 0.95 mg/mL and 1.29 mg/mL. These vials require preparation of dilutions prior to administration to patients intravenously.

CLINICAL PHARMACOLOGY

Milrinone lactate is a positive inotrope and vasodilator, with little chronotropic activity different in structure and mode of action from either the digitalis glycosides or catecholamines.

Milrinone lactate, at relevant inotropic and vasorelaxant concentrations, is a selective inhibitor of peak III cAMP phosphodiesterase isozyme in cardiac and vascular muscle. This inhibitory action is consistent with cAMP mediated increases in intracellular ionized calcium and contractile force in cardiac muscle, as well as with cAMP dependent contractile protein phosphorylation and relaxation in vascular muscle. Additional experimental evidence also indicates that milrinone lactate is not a beta-adrenergic agonist nor does it inhibit sodium-potassium adenosine triphosphatase activity as do the digitalis glycosides.

Clinical studies in patients with congestive heart failure have shown that milrinone lactate produces dose-related and plasma drug concentration-related increases in the maximum rate of increase of left ventricular pressure. Studies in normal subjects have shown that milrinone lactate produces increases in the slope of the left ventricular pressure-dimension relationship, indicating a direct inotropic effect of the drug. Milrinone lactate also produces dose-related and plasma concentration-related increases in forearm blood flow in patients with congestive heart failure, indicating a direct arterial vasodilator activity of the drug.

Both the inotropic and vasodilatory effects have been observed over the therapeutic range of plasma milrinone concentrations of 100 ng/mL to 300 ng/mL.

In addition to increasing myocardial contractility, milrinone lactate improves diastolic function as evidenced by improvements in left ventricular diastolic relaxation.

The acute administration of intravenous milrinone has also been evaluated in clinical trials in excess of 1600 patients, with chronic heart failure, heart failure associated with cardiac surgery, and heart failure associated with myocardial infarction. The total number of deaths, either on therapy or shortly thereafter (24 hours) was 15, less than 0.9%, few of which were thought to be drug-related.

PHARMACOKINETICS

Following intravenous injections of 12.5 mcg/kg to 125 mcg/kg to congestive heart failure patients, milrinone lactate had a volume of distribution of 0.38 liters/kg, a mean terminal elimination half-life of 2.3 hours, and a clearance of 0.13 liters/kg/hr. Following intravenous infusions of 0.2 mcg/kg/min to 0.7 mcg/kg/min to congestive heart failure patients, the drug had a volume of distribution of about 0.45 liters/kg, a mean terminal elimination half-life of 2.4 hours, and a clearance of 0.14 liters/kg/hr. These pharmacokinetic parameters were not dose-dependent, and the area under the plasma concentration versus time curve following injections was significantly dose-dependent.

Milrinone lactate has been shown (by equilibrium dialysis) to be approximately 70% bound to human plasma protein.

The primary route of excretion of milrinone lactate in man is via the urine. The major urinary excretions of orally administered milrinone lactate in man are milrinone (83%) and its 0-glucuronide metabolite (12%). Elimination in normal subjects via the urine is rapid, with approximately 60% recovered within the first two hours following dosing and approximately 90% recovered within the first eight hours following dosing. The mean renal clearance of milrinone lactate is approximately 0.3 liters/min, indicative of active secretion.

Pharmacodynamics

In patients with heart failure due to depressed myocardial function, milrinone lactate produced a prompt dose and plasma concentration related increase in cardiac output and decreases in pulmonary capillary wedge pressure and vascular resistance, which were accompanied by mild-to-moderate increases in heart rate. Additionally, there is no increased effect on myocardial oxygen consumption. In uncontrolled studies, hemodynamic improvement during intravenous therapy with milrinone lactate was accompanied by clinical symptomatic improvement, but the ability of milrinone lactate to relieve symptoms has not been evaluated in controlled clinical trials. The great majority of patients experience improvements in hemodynamic function within 5 to 15 minutes of the initiation of therapy.

In studies in congestive heart failure patients, milrinone lactate when administered as a loading injection followed by a maintenance infusion produced significant mean initial increases in cardiac index of 25 percent, 38 percent, and 42 percent at dose regimens of 37.5 mcg/kg/0.375 mcg/kg/min, 50 mcg/kg/0.5 mcg/kg/min, and 75 mcg/kg/0.75 mcg/kg/min, respectively. Over the same range of loading injections and maintenance infusions, pulmonary capillary wedge pressure significantly decreased by 20 percent, 23 percent, and 36 percent, respectively, while systemic vascular resistance significantly decreased by 17 percent, 21 percent, and 37 percent. Mean arterial pressure fell by up to 5 percent at the two lower dose regimens, but by 17 percent at the highest dose. Patients evaluated for 48 hours maintained improvements in hemodynamic function, with no evidence of diminished response (tachyphylaxis). A smaller number of patients have received infusions of milrinone lactate for periods up to 72 hours without evidence of tachyphylaxis.

The duration of therapy should depend upon patient responsiveness.

Milrinone lactate has a favorable inotropic effect in fully digitalized patients without causing signs of glycoside toxicity. Theoretically, in cases of atrial flutter/fibrillation, it is possible that milrinone lactate may increase ventricular response rate because of its slight enhancement of AV node conduction. In these cases, digitalis should be considered prior to the institution of therapy with milrinone lactate.

Improvement in left ventricular function in patients with ischemic heart disease has been observed. The improvement has occurred without inducing symptoms or electrocardiographic signs of myocardial ischemia.

The steady-state plasma milrinone concentrations after approximately 6 to 12 hours of unchanging maintenance infusion of 0.5 mcg/kg/min are approximately 200 ng/mL. Near maximum favorable effects of milrinone lactate on cardiac output and pulmonary capillary wedge pressure are seen at plasma milrinone concentrations in the 150 ng/mL to 250 ng/mL range.

INDICATIONS AND USAGE

Milrinone Lactate Injection is indicated for the short-term intravenous treatment of patients with acute decompensated heart failure. Patients receiving milrinone lactate should be observed closely with appropriate electrocardiographic equipment. The facility for immediate treatment of potential cardiac events, which may include life threatening ventricular arrhythmias, must be available. The majority of experience with intravenous milrinone lactate has been in patients receiving digoxin and diuretics.

CONTRAINDICATIONS

Milrinone Lactate Injection is contraindicated in patients who are hypersensitive to it.

WARNINGS

Whether given orally or by continuous or intermittent intravenous infusion, milrinone lactate has not been shown to be safe or effective in the longer (greater than 48 hours) treatment of patients with heart failure. In a multicenter trial of 1088 patients with Class III and IV heart failure, long-term oral treatment with milrinone lactate was associated with no improvement in symptoms and an increased risk of hospitalization and death. In this study, patients with Class IV symptoms appeared to be at particular risk of life-threatening cardiovascular reactions. There is no evidence that milrinone lactate given by long-term continuous or intermittent infusion does not carry a similar risk.

The use of milrinone lactate both intravenously and orally has been associated with increased frequency of ventricular arrhythmias, including nonsustained ventricular tachycardia. Long-term oral use has been associated with an increased risk of sudden death. Hence, patients receiving milrinone lactate should be observed closely with the use of continuous electrocardiographic monitoring to allow the prompt detection and management of ventricular arrhythmias.

PRECAUTIONS

General

Milrinone lactate should not be used in patients with severe obstructive aortic or pulmonic valvular disease in lieu of surgical relief of the obstruction. Like other inotropic agents, it may aggravate outflow tract obstruction in hypertrophic subaortic stenosis.

Supraventricular and ventricular arrhythmias have been observed in the high-risk population treated. In some patients, injections of milrinone lactate and oral milrinone lactate have been shown to increase ventricular ectopy, including nonsustained ventricular tachycardia. The potential for arrhythmia, present in congestive heart failure itself, may be increased by many drugs or combinations of drugs. Patients receiving milrinone lactate should be closely monitored during infusion.

Milrinone lactate produces a slight shortening of AV node conduction time, indicating a potential for an increased ventricular response rate in patients with atrial flutter/fibrillation which is not controlled with digitalis therapy.

During therapy with milrinone lactate, blood pressure and heart rate should be monitored and the rate of infusion slowed or stopped in patients showing excessive decreases in blood pressure.

If prior vigorous diuretic therapy is suspected to have caused significant decreases in cardiac filling pressure, milrinone lactate should be cautiously administered with monitoring of blood pressure, heart rate, and clinical symptomatology.

There is no experience in controlled trials with infusions of milrinone for periods exceeding 48 hours. Cases of infusion site reaction have been reported with intravenous milrinone therapy (see ADVERSE REACTIONS). Consequently, careful monitoring of the infusion site should be maintained to avoid possible extravasation.

Use in Acute Myocardial Infarction

No clinical studies have been conducted in patients in the acute phase of post myocardial infarction. Until further clinical experience with this class of drugs is gained, milrinone lactate is not recommended in these patients.

Laboratory Tests

Fluid and Electrolytes: Fluid and electrolyte changes and renal function should be carefully monitored during therapy with milrinone lactate. Improvement in cardiac output with resultant diuresis may necessitate a reduction in the dose of diuretic. Potassium loss due to excessive diuresis may predispose digitalized patients to arrhythmias. Therefore, hypokalemia should be corrected by potassium supplementation in advance of or during use of milrinone lactate.

Drug Interactions

No untoward clinical manifestations have been observed in limited experience with patients in whom milrinone lactate was used concurrently with the following drugs: digitalis glycosides; lidocaine, quinidine; hydralazine, prazosin; isosorbide dinitrate, nitroglycerin; chlorthalidone, furosemide, hydrochlorothiazide, spironolactone; captopril; heparin, warfarin, diazepam, insulin; and potassium supplements.

Chemical Interactions

There is an immediate chemical interaction which is evidenced by the formation of a precipitate when furosemide is injected into an intravenous line of an infusion of milrinone lactate. Therefore, furosemide should not be administered in intravenous lines containing milrinone lactate.

Carcinogenesis, Mutagenesis, Impairment of Fertility

Twenty-four months of oral administration of milrinone lactate to mice at doses up to 40 mg/kg/day (about 50 times the human oral therapeutic dose in a 50 kg patient) was unassociated with evidence of carcinogenic potential. Neither was there evidence of carcinogenic potential when milrinone lactate was orally administered to rats at doses up to 5 mg/kg/day (about 6 times the human oral therapeutic dose) for twenty-four months or at 25 mg/kg/day (about 30 times the human oral therapeutic dose) for up to 18 months in males and 20 months in females. Whereas the Chinese Hamster Ovary Chromosome Aberration Assay was positive in the presence of a metabolic activation system, results from the Ames Test, the Mouse Lymphoma Assay, the Micronucleus Test, and the in vivo Rat Bone Marrow Metaphase Analysis indicated an absence of mutagenic potential. In reproductive performance studies in rats, milrinone lactate had no effect on male or female fertility at oral doses up to 32 mg/kg/day.

Animal Toxicity

Oral and intravenous administration of toxic dosages of milrinone lactate to rats and dogs resulted in myocardial degeneration/fibrosis and endocardial hemorrhage, principally affecting the left ventricular papillary muscles. Coronary vascular lesions characterized by periarterial edema and inflammation have been observed in dogs only. The myocardial/endocardial changes are similar to those produced by beta-adrenergic receptor agonists such as isoproterenol, while the vascular changes are similar to those produced by minoxidil and hydralazine. Doses within the recommended clinical dose range (up to 1.13 mg/kg/day) for congestive heart failure patients have not produced significant adverse effects in animals.

Pregnancy

Oral administration of milrinone lactate to pregnant rats and rabbits during organogenesis produced no evidence of teratogenicity at dose levels up to 40 mg/kg/day and 12 mg/kg/day, respectively. Milrinone lactate did not appear to be teratogenic when administered intravenously to pregnant rats at doses up to 3 mg/kg/day (about 2.5 times the maximum recommended clinical intravenous dose) or pregnant rabbits at doses up to 12 mg/kg/day, although an increased resorption rate was apparent at both 8 mg/kg/day and 12 mg/kg/day (intravenous) in the latter species. There are no adequate and well-controlled studies in pregnant women. Milrinone lactate should be used during pregnancy only if the potential benefit justifies the potential risk to the fetus.

Nursing Mothers

Caution should be exercised when milrinone lactate is administered to nursing women, since it is not known whether it is excreted in human milk.

Pediatric Use

Safety and effectiveness in pediatric patients have not been established.

Use in Elderly Patients

There are no special dosage recommendations for the elderly patient. Ninety percent of all patients administered milrinone lactate in clinical studies were within the age range of 45 to 70 years, with a mean age of 61 years. Patients in all age groups demonstrated clinically and statistically significant responses. No age-related effects on the incidence of adverse reactions have been observed. Controlled pharmacokinetic studies have not disclosed any age-related effects on the distribution and elimination of milrinone lactate.

ADVERSE REACTIONS

Cardiovascular Effects

In patients receiving milrinone lactate in Phase II and III clinical trials, ventricular arrhythmias were reported in 12.1%: Ventricular ectopic activity, 8.5%; nonsustained ventricular tachycardia, 2.8%; sustained ventricular tachycardia, 1% and ventricular fibrillation, 0.2% (2 patients experienced more than one type of arrhythmia). Holter recordings demonstrated that in some patients injection of milrinone lactate increased ventricular ectopy, including nonsustained ventricular tachycardia. Life-threatening arrhythmias were infrequent and when present have been associated with certain underlying factors such as preexisting arrhythmias, metabolic abnormalities (e.g. hypokalemia), abnormal digoxin levels and catheter insertion. Milrinone lactate was not shown to be arrhythmogenic in an electrophysiology study. Supraventricular arrhythmias were reported in 3.8% of the patients receiving milrinone lactate. The incidence of both supraventricular and ventricular arrhythmias has not been related to the dose or plasma milrinone concentration.

Other cardiovascular adverse reactions include hypotension, 2.9% and angina/chest pain, 1.2%.

In the post marketing experience, there have been rare cases of “torsades de pointes” reported.

CNS Effects

Headaches, usually mild to moderate in severity, have been reported in 2.9% of patients receiving milrinone lactate.

Other Effects

Other adverse reactions reported, but not definitely related to the administration of milrinone lactate include hypokalemia, 0.6%; tremor, 0.4%; and thrombocytopenia, 0.4%.

Isolated spontaneous reports of bronchospasm and anaphylactic shock have been received; and in the post-marketing experience, liver function test abnormalities and skin reactions such as rash have been reported.

Post-Marketing Adverse Event Reports

In addition to adverse events reported from clinical trials, the following events have been reported from worldwide post-marketing experience with milrinone: Isolated spontaneous reports of bronchospasm and anaphylactic shock. Liver function test abnormalities and skin reactions such as rash. Administration site conditions: Infusion site reaction. To report SUSPECTED ADVERSE REACTIONS, contact Shandong New Time Pharmaceutical Co., Ltd., at 1-866-XXX-XXXX or FDA at 1-800-FDA-1088 or www.fda.gov/medwatch.

OVERDOSAGE

Doses of milrinone lactate may produce hypotension because of its vasodilator effect. If this occurs, administration of milrinone lactate should be reduced or temporarily discontinued until the patient’s condition stabilizes. No specific antidote is known, but general measures for circulatory support should be taken.

DOSAGE AND ADMINISTRATION

Milrinone Lactate Injection, USP should be administered with a loading dose followed by a continuous infusion (maintenance dose) according to the following guidelines:

LOADING DOSE

50 mcg/kg: Administer slowly over 10 minutes

The table below shows the loading dose in milliliters (mL) of milrinone lactate (1mg/mL) by patient body weight (kg).
Loading Dose (mL) Using 1 mg/mL Concentration
Patient Body Weight (kg)
kg | 30 | 40 | 50 | 60 | 70 | 80 | 90 | 100 | 110 | 120
mL | 1.5 | 2 | 2.5 | 3 | 3.5 | 4 | 4.5 | 5 | 5.5 | 6

The loading dose may be given undiluted, but diluting to a rounded total volume of 10 or 20 mL (see Maintenance Dose for diluents) may simplify the visualization of the injection rate.

MAINTENANCE DOSE
 | Infusion Rate | Total Daily Dose (24 Hours)
Minimum | 0.375 mcg/kg/min | 0.59 mg/kg | Administer as a continuous intravenous infusion
Standard | 0.5 mcg/kg/min | 0.77 mg/kg | Administer as a continuous intravenous infusion
Maximum | 0.75 mcg/kg/min | 1.13 mg/kg | Administer as a continuous intravenous infusion

Milrinone lactate drawn from vials should be diluted prior to maintenance dose administration. The diluents that may be used are 0.45% Sodium Chloride Injection USP, 0.9% Sodium Chloride Injection USP, or 5% Dextrose Injection USP. The table below shows the volume of diluent in milliliters (mL) that must be used to achieve 200 mcg/mL concentration for infusion, and the resultant total volumes.

Desired Infusion Concentration mcg/mL | Milrinone Lactate Injection 1 mg/mL (mL) | Diluent (mL) | Total Volume (mL)
200 | 10 | 40 | 50
200 | 20 | 80 | 100

The infusion rate should be adjusted according to hemodynamic and clinical response. Patients should be closely monitored. In controlled clinical studies, most patients showed an improvement in hemodynamic status as evidenced by increases in cardiac output and reductions in pulmonary capillary wedge pressure.

Note: See Dosage Adjustment in Renally Impaired Patients. Dosage may be titrated to the maximum hemodynamic effect and should not exceed 1.13 mg/kg/day. Duration of therapy should depend upon patient responsiveness.

The maintenance dose in mL/hr by patient body weight (kg) may be determined by reference to the following table.

Milrinone Infusion Rate (mL/hr) Using 200 mcg/mL Concentration
Maintenance Dose (mcg/kg/min) | Patient Body Weight (kg)
Maintenance Dose (mcg/kg/min) | 30 | 40 | 50 | 60 | 70 | 80 | 90 | 100 | 110 | 120
0.375 | 3.4 | 4.5 | 5.6 | 6.8 | 7.9 | 9 | 10.1 | 11.3 | 12.4 | 13.5
0.4 | 3.6 | 4.8 | 6 | 7.2 | 8.4 | 9.6 | 10.8 | 12 | 13.2 | 14.4
0.5 | 4.5 | 6 | 7.5 | 9 | 10.5 | 12 | 13.5 | 15 | 16.5 | 18
0.6 | 5.4 | 7.2 | 9 | 10.8 | 12.6 | 14.4 | 16.2 | 18 | 19.8 | 21.6
0.7 | 6.3 | 8.4 | 10.5 | 12.6 | 14.7 | 16.8 | 18.9 | 21 | 23.1 | 25.2
0.75 | 6.8 | 9 | 11.3 | 13.5 | 15.8 | 18 | 20.3 | 22.5 | 24.8 | 27

When administering milrinone lactate by continuous infusion, it is advisable to use a calibrated electronic infusion device.

Intravenous drug products should be inspected visually and should not be used if particulate matter or discoloration is present.

Dosage Adjustment in Renally Impaired Patients

Data obtained from patients with severe renal impairment (creatinine clearance = 0 to 30 mL/min) but without congestive heart failure have demonstrated that the presence of renal impairment significantly increases the terminal elimination half-life of milrinone lactate. Reductions in infusion rate may be necessary in patients with renal impairment. For patients with clinical evidence of renal impairment, the recommended infusion rate can be obtained from the following table:

Creatinine Clearance (mL/min/1.73m^2) | Infusion Rate (mcg/kg/min)
5 | 0.2
10 | 0.23
20 | 0.28
30 | 0.33
40 | 0.38
50 | 0.43

HOW SUPPLIED

Milrinone Lactate Injection, USP is supplied as 10 mL single-dose vials in a box of 10, NDC 42677-313-10; as 20 mL single-dose vials box of 10, NDC 42677-314-10, containing a sterile, clear, colorless to pale yellow solution. Each mL contains milrinone lactate equivalent to 1 mg milrinone.

Store at 20° to 25°C (68° to 77°F) [See USP Controlled Room Temperature]. Avoid freezing.

Discard unused portion.

Manufactured by:
Shandong New Time Pharmaceutical Co., Ltd.,
No. 1, North Outer Ring Road,
Feixian, Shandong 273400, China.
Revised: 08/2022
LBL 128

PRINCIPAL DISPLAY PANEL -10 mL Vial Container and Carton

10 mL Vial Container

Milrinone Lactate Injection

10 mg/ 10 mL (1 mg/mL)

NDC 42677-313-01

Rx only

For Intravenous Use Only

10 mL Vial Carton

Milrinone Lactate Injection

10 mg/ 10 mL (1 mg/mL)

NDC 42677-313-10

Rx only

For Intravenous Use Only

PRINCIPAL DISPLAY PANEL -20 mL Vial Container and Carton

20 mL Vial Container

Milrinone Lactate Injection

20 mg/ 20 mL (1 mg/mL)

NDC 42677-314-01

Rx only

For Intravenous Use Only

20 mL Vial Carton

Milrinone Lactate Injection

20 mg/ 20 mL (1 mg/mL)

NDC 42677-314-10

Rx only

For Intravenous Use Only